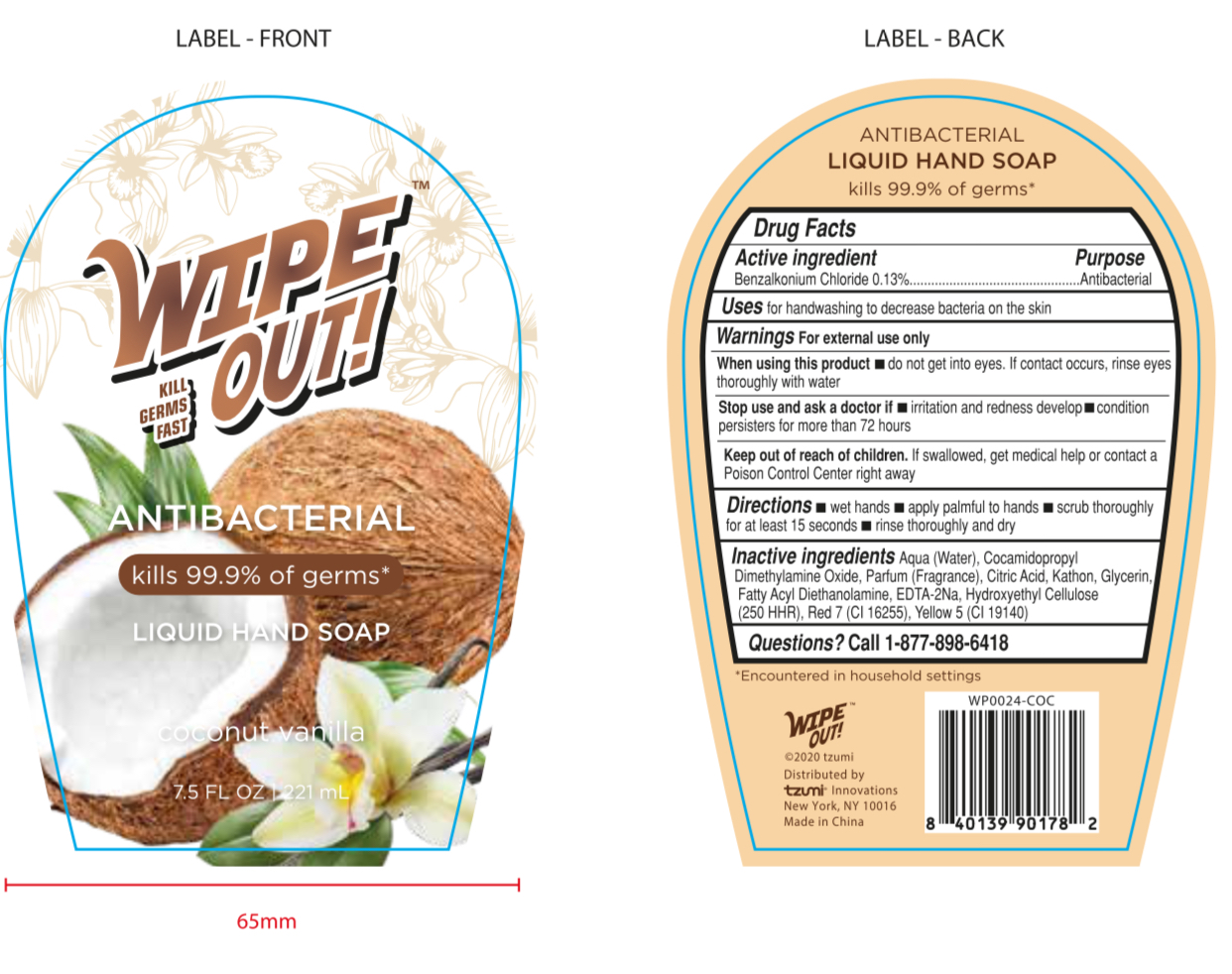 DRUG LABEL: WIPE OUT ANTIBACTERIAL Liquid Hand coconut vanilla
NDC: 77878-027 | Form: SOAP
Manufacturer: TZUMI INNOVATIONS LLC
Category: otc | Type: HUMAN OTC DRUG LABEL
Date: 20201223

ACTIVE INGREDIENTS: BENZALKONIUM CHLORIDE 0.13 g/100 mL
INACTIVE INGREDIENTS: HYDROXYETHYL CELLULOSE, UNSPECIFIED; D&C RED NO. 7; FD&C YELLOW NO. 5; WATER; CITRIC ACID MONOHYDRATE; GLYCERIN; DISODIUM HEDTA

77878-027, Style: WP0024 COC

Active Ingredient(s)

Benzalkonium Chloride 0.13%

Purpose

Antibacterial

Use

For hand washing to decrease bacteria on the skin

Warnings

For external use only

When using this product do not get into eyes. If contact occurs, rinse eyes thoroughly with water

Stop use and ask a doctor if irritation and redness develop, condition persists for more than 72 hours

Keep out of reach of children. If swallowed, get medical help or contact a Poison Control Center right away.

Directions

- Wet hands
- Apply palmful to hands
- Scrub thoroughly for at least 15 seconds
- Rinse thoroughly and dry

Inactive ingredients

Water, Cocamidopropyl dimethylamine oxide, Citric Acid, Fragrance, Kathon, Glycerin, Fatty acyl diethanol amine, Disodium EDTA, Hydroxyethyl Cellulose (250HHR), Red 7 (CI 16255), Yellow 5 (CI 19140)